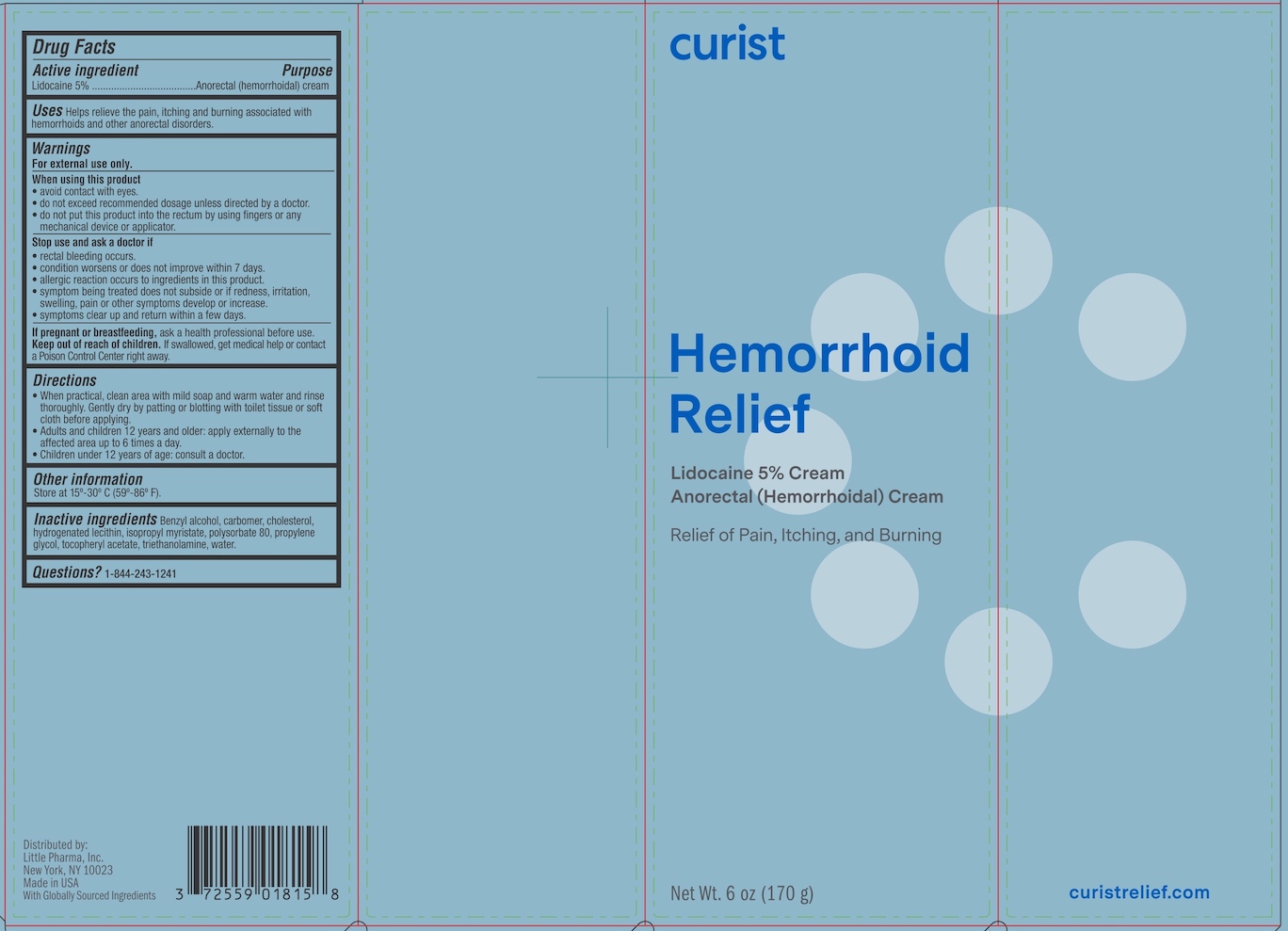 DRUG LABEL: Curist Hemorrhoid Relief
NDC: 72559-018 | Form: CREAM
Manufacturer: Little Pharma, Inc.
Category: otc | Type: HUMAN OTC DRUG LABEL
Date: 20251208

ACTIVE INGREDIENTS: LIDOCAINE 5 g/100 g
INACTIVE INGREDIENTS: HYDROGENATED SOYBEAN LECITHIN; WATER; CARBOMER 940; PROPYLENE GLYCOL; BENZYL ALCOHOL; .ALPHA.-TOCOPHEROL ACETATE; CHOLESTEROL; ISOPROPYL MYRISTATE; POLYSORBATE 80; TROLAMINE

Curist Hemorroid Relief

Drug Facts

Active ingredient

Lidocaine 5%

Purpose

Anorectal (hemorrhoidal) cream

Uses

Helps relieve the pain, itching and burning associated with hemorrhoids and other anorectal disorders.

Warnings

For external use only.

When using this product

- avoid contact with eyes.
- do not exceed recommended dosage unless directed by a doctor.
- do not put this product into the rectum by using fingers or any mechanical device or applicator.

Stop use and ask a doctor if

- rectal bleeding occurs.
- condition worsens or does not improve within 7 days.
- allergic reaction occurs to ingredients in this product.
- symptom being treated does not subside or if redness, irritation, swelling, pain or other symptoms develop or increase.
- symptoms clear up and return within a few days.

PREGNANCY OR BREAST FEEDING

If pregnant or breastfeeding, ask a health professional before use.

Keep out of reach of children. If swallowed, get medical help or contact a Poison Control Center right away.

Directions

- When practical, clean the affected area with mild soap and warm water and rinse thoroughly. Gently dry by patting or blotting with toilet tissue or soft cloth before applying.
- Adults and children 12 years and older: apply externally to the affected area up to 6 times a day.
- Children under 12 years of age: consult a doctor.

Other information

Store at 15-30°C (59-86°F)

INACTIVE INGREDIENT

Inactive ingredients Benzyl alcohol, carbomer, cholesterol, hydrogenated lecithin, isopropyl myristate, polysorbate 80, propylene glycol, tocopheryl acetate, triethanolamine, water.

Questions? 1-844-243-1241

Distributed by:

Little Pharma, Inc.

New York, NY 10023

Made in USA With Globally Sourced Ingredients

PACKAGE LABEL

curist

Hemorrhoid Relief

Lidocaine 5% Cream

Anorectal (Hemorrhoidal) Cream

Relief of Pain, Itching and Burning

Net. Wt. 6 oz (170 g)